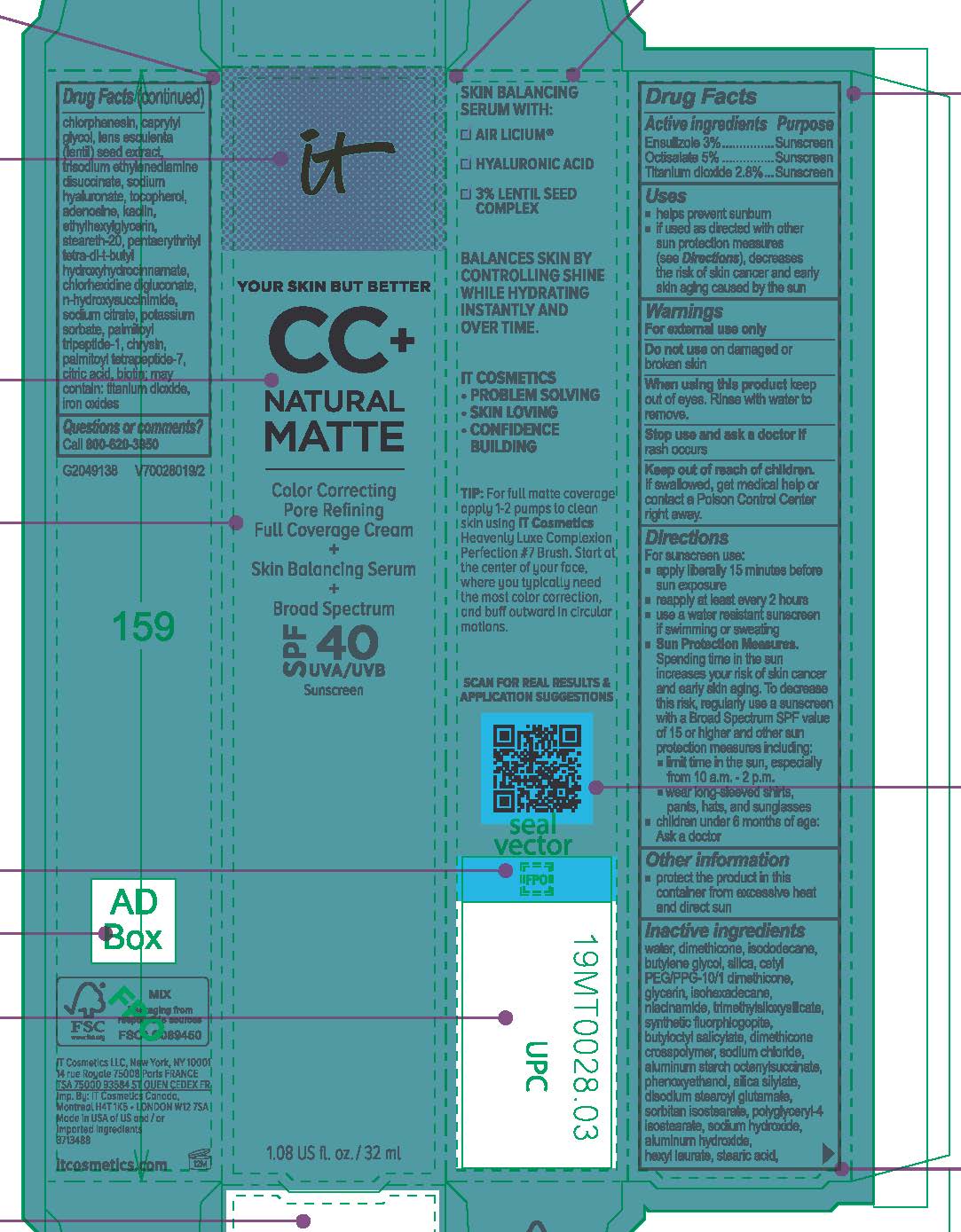 DRUG LABEL: it cosmetics Your Skin But Better CC Plus Natural Matte Color Correcting Pore Refining Full Coverage Skin Balancing Serum Broad Spectrum SPF 40 Sunscreen
NDC: 69259-3488 | Form: CREAM
Manufacturer: IT COSMETICS, LLC
Category: otc | Type: HUMAN OTC DRUG LABEL
Date: 20241229

ACTIVE INGREDIENTS: OCTISALATE 50 mg/1 mL; TITANIUM DIOXIDE 28 mg/1 mL; ENSULIZOLE 30 mg/1 mL
INACTIVE INGREDIENTS: WATER; DIMETHICONE; ISODODECANE; BUTYLENE GLYCOL; SILICON DIOXIDE; CETYL PEG/PPG-10/1 DIMETHICONE (HLB 4); GLYCERIN; ISOHEXADECANE; NIACINAMIDE; TRIMETHYLSILOXYSILICATE (M/Q 0.6-0.8); MAGNESIUM POTASSIUM ALUMINOSILICATE FLUORIDE; BUTYLOCTYL SALICYLATE; DIMETHICONE CROSSPOLYMER (450000 MPA.S AT 12% IN CYCLOPENTASILOXANE); SODIUM CHLORIDE; ALUMINUM STARCH OCTENYLSUCCINATE; PHENOXYETHANOL; DISODIUM STEAROYL GLUTAMATE; SORBITAN ISOSTEARATE; POLYGLYCERYL-4 ISOSTEARATE; SODIUM HYDROXIDE; ALUMINUM HYDROXIDE; HEXYL LAURATE; STEARIC ACID; CHLORPHENESIN; CAPRYLYL GLYCOL; LENTIL; TRISODIUM ETHYLENEDIAMINE DISUCCINATE; HYALURONATE SODIUM; TOCOPHEROL; ADENOSINE; KAOLIN; ETHYLHEXYLGLYCERIN; STEARETH-20; PENTAERYTHRITOL TETRAKIS(3-(3,5-DI-TERT-BUTYL-4-HYDROXYPHENYL)PROPIONATE); CHLORHEXIDINE GLUCONATE; N-HYDROXYSUCCINIMIDE; SODIUM CITRATE; POTASSIUM SORBATE; PALMITOYL TRIPEPTIDE-1; CHRYSIN; PALMITOYL TETRAPEPTIDE-7; CITRIC ACID MONOHYDRATE; BIOTIN; FERRIC OXIDE RED

Drug Facts

Active ingredients

Ensulizole 3%

Octisalate 5%

Titanium dioxide 2.8%

Purpose

Sunscreen

Uses

- helps prevent sunburn

- if used as directed with other sun protection measures (see Directions), decreases the risk of skin cancer and early skin aging caused by the sun

Warnings

For external use only

Do not use

on damaged or broken skin

When using this product

keep out of eyes. Rinse with water to remove.

Stop use and ask a doctor if

rash occurs

Keep out of reach of children.

If swallowed, get medical help or contact a Poison Control Center right away.

Directions

● shake well before use

● apply liberally 15 minutes before sun exposure

● reapply at least every 2 hours

● use a water resistant sunscreen if swimming or sweating

● Sun Protection Measures. Spending time in the sun increases your risk of skin cancer and early skin aging. To decrease this risk,

regularly use a sunscreen with a Broad Spectrum SPF value of 15 or higher and other sun protection measures including:

● limit time in the sun, especially from 10 a.m. – 2 p.m.

● wear long-sleeved shirts, pants, hats, and sunglasses

● children under 6 months of age: Ask a doctor

Other information

protect the product in this container from excessive heat and direct sun

Inactive ingredients

water, dimethicone, isododecane, butylene glycol, silica, cetyl PEG/PPG-10/1 dimethicone, glycerin, isohexadecane, niacinamide, trimethylsiloxysilicate, synthetic fluorphlogopite, butyloctyl salicylate, dimethicone crosspolymer, sodium chloride, aluminum starch octenylsuccinate, phenoxyethanol, silica silylate, disodium stearoyl glutamate, sorbitan isostearate, polyglyceryl-4 isostearate, sodium hydroxide, aluminum hydroxide, hexyl laurate, stearic acid, chlorphenesin, caprylyl glycol, lens esculenta (lentil) seed extract, trisodium ethylenediamine disuccinate, sodium hyaluronate, tocopherol, adenosine, kaolin, ethylhexylglycerin, steareth-20, pentaerythrityl tetra-di-t-butyl hydroxyhydrocinnamate, chlorhexidine digluconate, n-hydroxysuccinimide, sodium citrate, potassium sorbate, palmitoyl tripeptide-1, chrysin, palmitoyl tetrapeptide-7, citric acid, biotin; may contain titanium dioxide, iron oxides

Questions or comments?

Call 800-620-3950